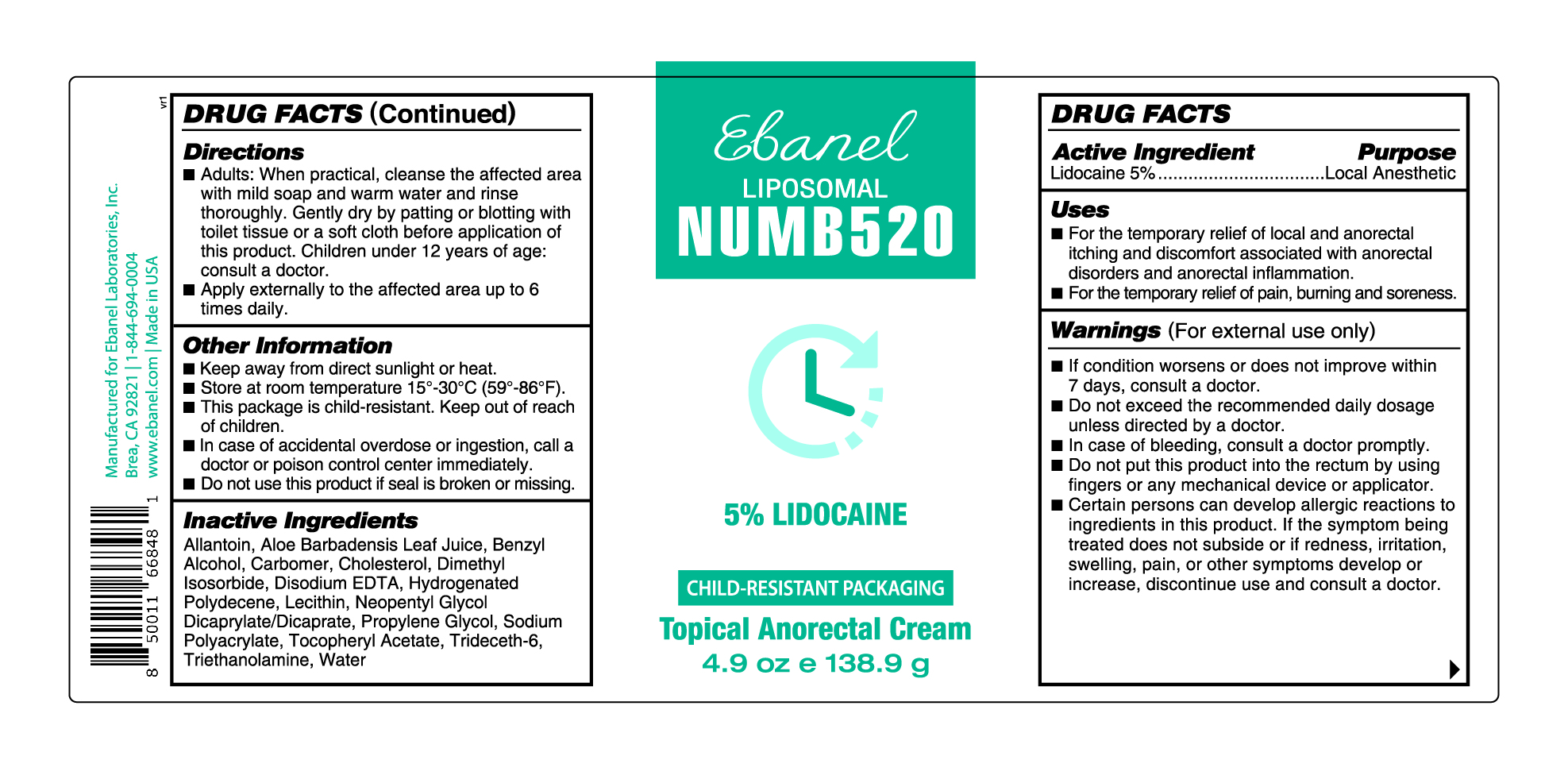 DRUG LABEL: Numb 520
NDC: 72654-027 | Form: CREAM
Manufacturer: Ebanel Laboratories, Inc
Category: otc | Type: HUMAN OTC DRUG LABEL
Date: 20250604

ACTIVE INGREDIENTS: LIDOCAINE 5 mg/1 g
INACTIVE INGREDIENTS: TRIETHANOLAMINE; PROPYLENE GLYCOL; SODIUM POLYACRYLATE (2500000 MW); HYDROGENATED POLYDECENE (1500 CST); LECITHIN, SOYBEAN; TRIDECETH-6; CHOLESTEROL; ALOE BARBADENSIS LEAF JUICE; .ALPHA.-TOCOPHEROL ACETATE, D-; WATER; BENZYL ALCOHOL; CARBOMER; DIMETHYL ISOSORBIDE; NEOPENTYL GLYCOL DICAPRYLATE/DICAPRATE; DISODIUM EDTA-COPPER; ALLANTOIN

Active Ingredient - Lidocaine 5%

DOSAGE AND ADMINISTRATION

■ Adults: When practical, cleanse the affected area with mild soap and warm water and rinse thoroughly. Gently dry by patting or blotting with toilet tissue or a soft cloth before application of this product. Children under 12 years of age: consult a doctor.

■ Apply externally to the affected area up to 6 times daily.

Warnings (For external use only)

■ If condition worsens or does not improve within 7 days, consult a doctor.

■ Do not exceed the recommended daily dosage unless directed by a doctor.

■ In case of bleeding, consult a doctor promptly.

■ Do not put this product into the rectum by using fingers or any mechanical device or applicator.

■ Certain persons can develop allergic reactions to ingredients in this product. If the symptom being treated does not subside or if redness, irritation, swelling, pain, or other symptoms develop or increase, discontinue use and consult a doctor.

Uses

■ For the temporary relief of local and anorectal itching and discomfort associated with anorectal disorders and anorectal inflammation.

■ For the temporary relief of pain, burning and soreness.

Other Information

■ Keep away from direct sunlight or heat.

■ Store at room temperature 15°-30°C (59°-86°F).

■ This package is child-resistant. Keep out of reach of children.

■ In case of accidental overdose or ingestion, call a doctor or poison control center immediately.

■ Do not use this product if seal is broken or missing.

Inactive Ingredients

Allantoin, Aloe Barbadensis Leaf Juice, Benzyl Alcohol, Carbomer, Cholesterol, Dimethyl Isosorbide, Disodium EDTA, Hydrogenated Polydecene, Lecithin, Neopentyl Glycol Dicaprylate/Dicaprate, Propylene Glycol, Sodium Polyacrylate, Tocopheryl Acetate, Trideceth-6, Triethanolamine, Water

Purpose………………………………………….Local Anesthetic